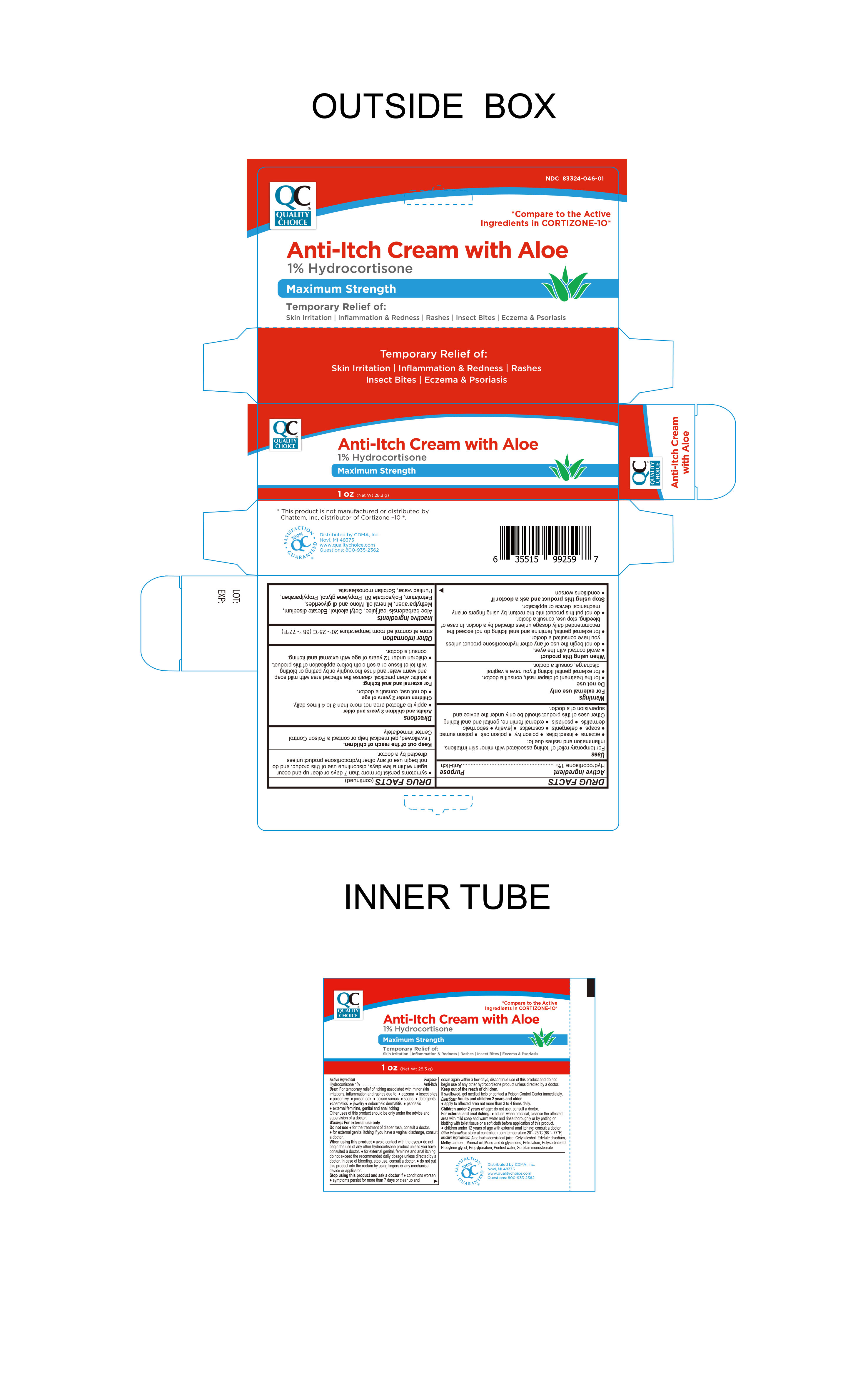 DRUG LABEL: Anti-Itch with Aloe
NDC: 83324-046 | Form: CREAM
Manufacturer: Chain Drug Marketing Association Inc.
Category: otc | Type: HUMAN OTC DRUG LABEL
Date: 20240708

ACTIVE INGREDIENTS: HYDROCORTISONE 1 g/100 g
INACTIVE INGREDIENTS: SORBITAN MONOSTEARATE; ALOE VERA LEAF; EDETATE DISODIUM; POLYSORBATE 60; WATER; CETYL ALCOHOL; PETROLATUM; MINERAL OIL; METHYLPARABEN; PROPYLENE GLYCOL; GLYCERYL MONO AND DIPALMITOSTEARATE; PROPYLPARABEN

Quality Choice Anti-Itch Cream with Aloe

Active Ingredient

Hydrocortisone 1%

Purpose

Anti-Itch

INDICATIONS AND USAGE

For the temporary relief of itching associated with minor skin irritations, inflammation and rashes due to

- insect bites
- eczema
- poison ivy
- poison oak
- poison sumac
- soaps
- detergents
- cosmetics
- jewelry
- seborrheic dermatitis
- psoriasis
- external feminine genital and anal itching
- Other uses of this product should be only under the advice and supervision of a doctor.

Warnings

For External Use Only

Do not usefor the treatment of diaper rash, consult a doctor.

For external genital itching if you have a vaginal discharge, consult a doctor.

Stop use and ask a doctor

- Conditions worsen
- Symptoms persist for more than 7 days or clear up and occur again within a few days, discontinue use of this product and do not begin use of any other hydrocortisone product unless directed by a doctor.

Keep out of the reach of children

If swallowed, get medical help or contact a Poison Control Center immediately

Other information

- Store at controlled room temperature 20º-25ºC (68º-77ºF)

Inactive Ingredients

Aloe Vera (Aloe Barbadensis) leaf juice, Cetyl alcohol, Edatate Disodium, Methylparaben, Mineral Oil, Petrolatum, Propylene glycol, Purified Water, Sorbitan Monostearate, Polysorbate 60, propylparaban, mono and di glycerides.

When using this product

- Avoid contact with the eyes
- do not begin the use of any other hydrocortisone product unless you have consulted a doctor.
- for external genital, feminine and anal itching do not exceed the recommended daily dosage unless directed by a doctor. In the case of bleeding, stop use, consult a doctor.
- do not put this product into the rectum by using fingers or any mechanical device or applicator.

Directions

Adults and children 2 years and older

- apply to affected area not more than 3 to 4 times daily.

Children under 2 years of age

- do not use, consult doctor

For external and anal itching

- adults when practical cleanse the affected area with mild soap and warm water and rinse thoroughly or by patting or blotting with toilet tissue or a soft cloth before application of this product.

- Children under 12 years of age with external anal ithcing consult a doctor.

Distributed By

Distributed By CDMA Inc.

43157 W 9 Mile Rd.

Novi, MI. 48375

www.qualitychoice.com

Questions: 800-935-2362

Product PRC